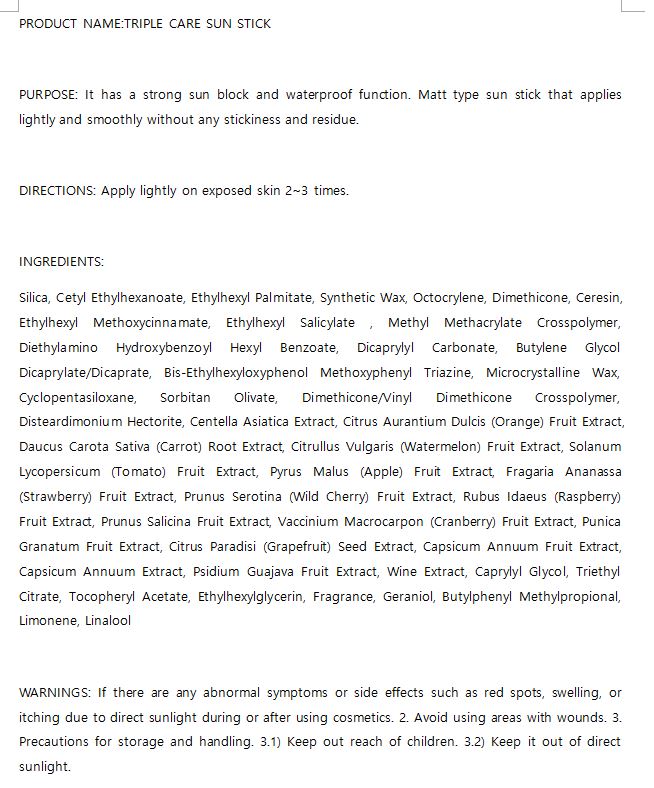 DRUG LABEL: W.SKIN TRIPLE CARE SUN
NDC: 74997-0015 | Form: STICK
Manufacturer: J&J COMPANY
Category: otc | Type: HUMAN OTC DRUG LABEL
Date: 20210507

ACTIVE INGREDIENTS: OCTOCRYLENE 8.5 g/100 g
INACTIVE INGREDIENTS: GLYCERIN; WATER

J&J COMPANY - STOP-AGING PEPTIDE TONER

ACTIVE INGREDIENT

Octocrylene

INACTIVE INGREDIENT

Cetyl Ethylhexanoate, Ethylhexyl Palmitate, Synthetic Wax, Octocrylene, Dimethicone, Ceresin, Ethylhexyl Methoxycinnamate, Ethylhexyl Salicylate , Methyl Methacrylate Crosspolymer, Diethylamino Hydroxybenzoyl Hexyl Benzoate, Dicaprylyl Carbonate, Butylene Glycol Dicaprylate/Dicaprate, Bis-Ethylhexyloxyphenol Methoxyphenyl Triazine, Microcrystalline Wax, Cyclopentasiloxane, Sorbitan Olivate, Dimethicone/Vinyl Dimethicone Crosspolymer, Disteardimonium Hectorite, Centella Asiatica Extract, Citrus Aurantium Dulcis (Orange) Fruit Extract, Daucus Carota Sativa (Carrot) Root Extract, Citrullus Vulgaris (Watermelon) Fruit Extract, Solanum Lycopersicum (Tomato) Fruit Extract, Pyrus Malus (Apple) Fruit Extract, Fragaria Ananassa (Strawberry) Fruit Extract, Prunus Serotina (Wild Cherry) Fruit Extract, Rubus Idaeus (Raspberry) Fruit Extract, Prunus Salicina Fruit Extract, Vaccinium Macrocarpon (Cranberry) Fruit Extract, Punica Granatum Fruit Extract, Citrus Paradisi (Grapefruit) Seed Extract, Capsicum Annuum Fruit Extract, Capsicum Annuum Extract, Psidium Guajava Fruit Extract, Wine Extract, Caprylyl Glycol, Triethyl Citrate, Tocopheryl Acetate, Ethylhexylglycerin, Fragrance, Geraniol, Butylphenyl Methylpropional, Limonene, Linalool

PURPOSE

It has a strong sun block and waterproof function. Matt type sun stick that applies lightly and smoothly without any stickiness and residue.

keep out of reach of the children

INDICATIONS AND USAGE

Apply lightly on exposed skin 2~3 times

WARNINGS

If there are any abnormal symptoms or side effects such as red spots, swelling, or itching due to direct sunlight during or after using cosmetics. 2. Avoid using areas with wounds. 3. Precautions for storage and handling. 3.1) Keep out reach of children. 3.2) Keep it out of direct sunlight.

DOSAGE AND ADMINISTRATION

for external use only